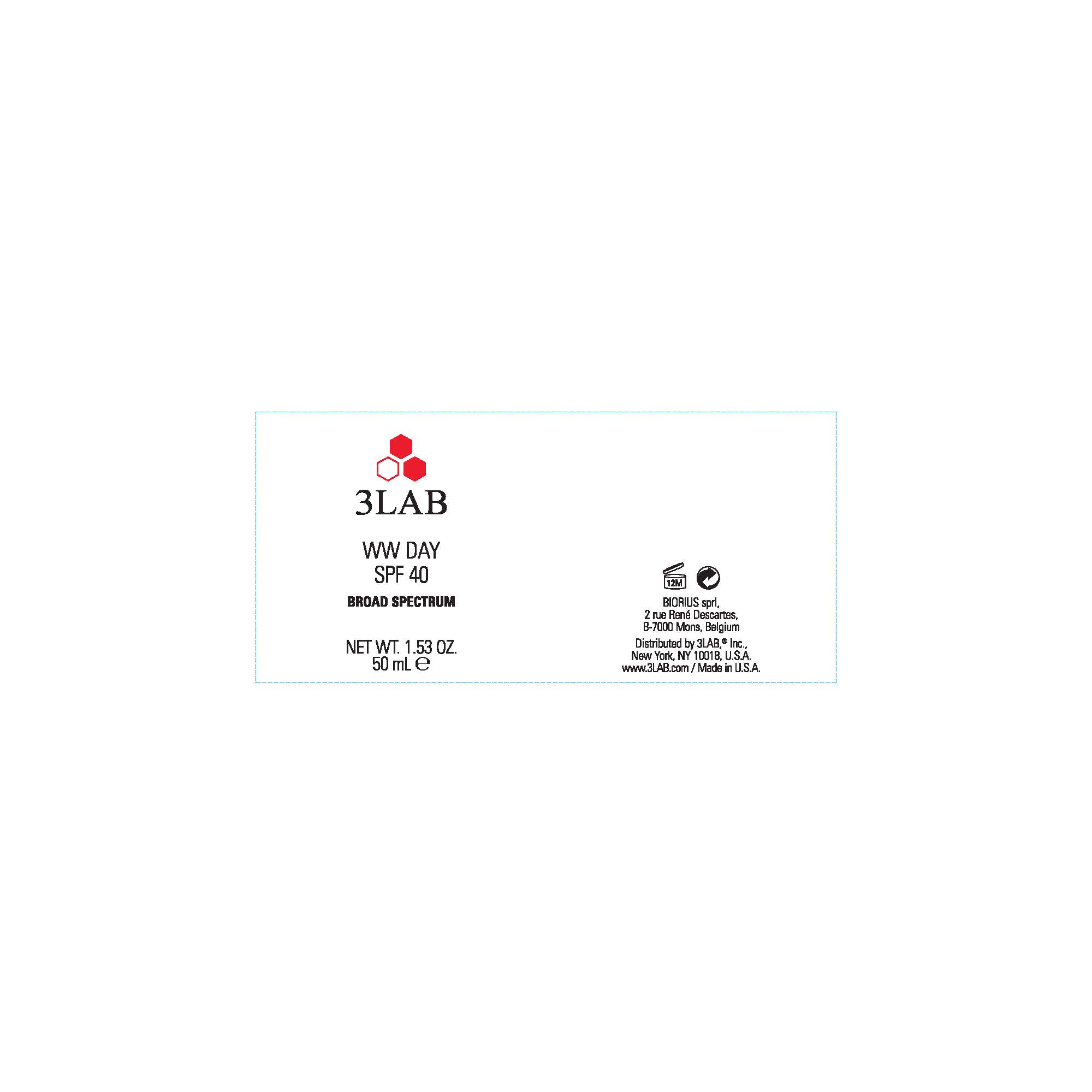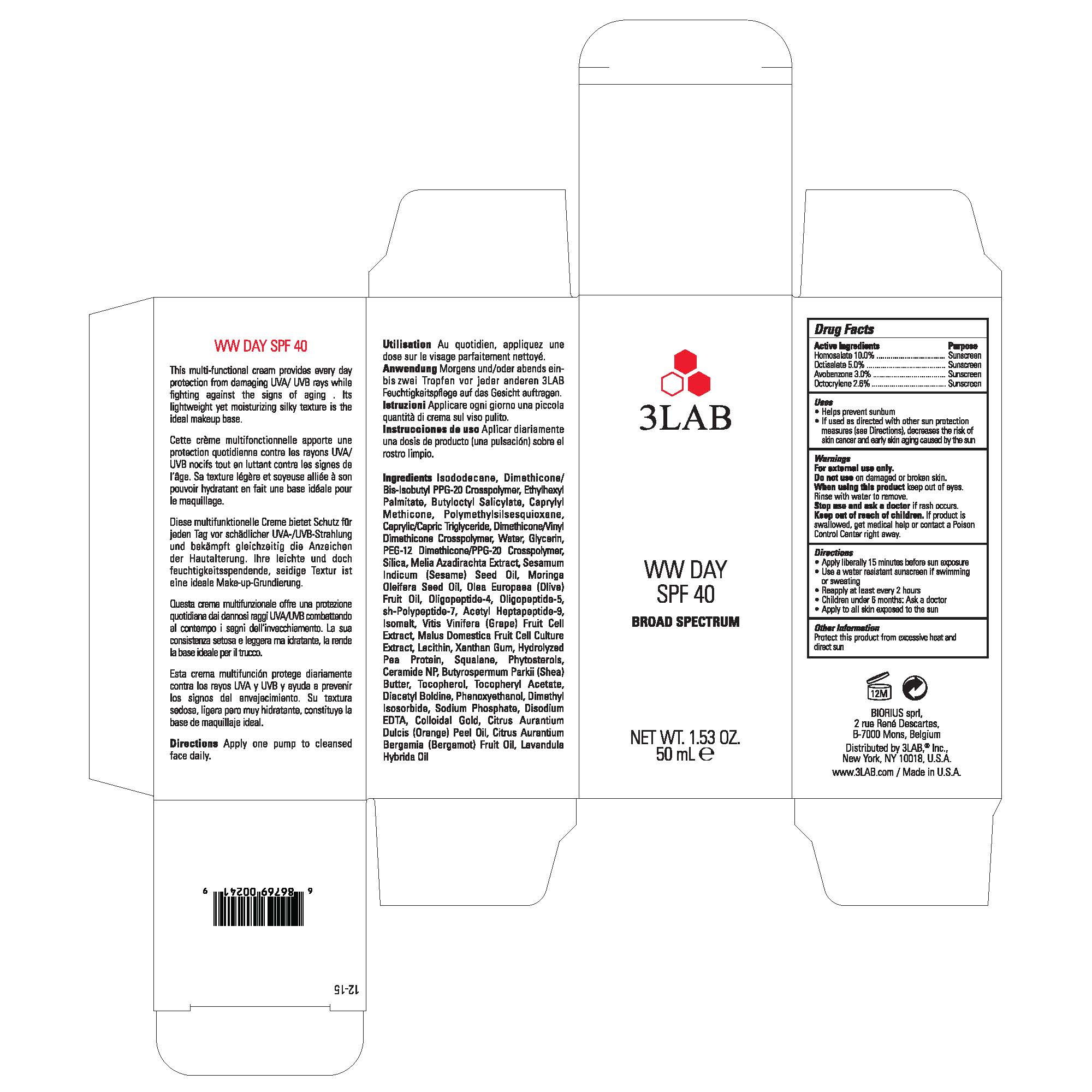 DRUG LABEL: 3LAB WW DAY SPF40 BROAD SPECTRUM
NDC: 76159-205 | Form: CREAM
Manufacturer: 3LAB, INC
Category: otc | Type: HUMAN OTC DRUG LABEL
Date: 20241226

ACTIVE INGREDIENTS: HOMOSALATE 10 mg/100 mg; OCTISALATE 5 mg/100 mg; AVOBENZONE 3 mg/100 mg; OCTOCRYLENE 2.6 mg/100 mg
INACTIVE INGREDIENTS: DIMETHICONE/BIS-ISOBUTYL PPG-20 CROSSPOLYMER; SODIUM PHOSPHATE; SQUALANE; OLIVE OIL; GLYCERIN; DIMETHICONE/VINYL DIMETHICONE CROSSPOLYMER (HARD PARTICLE); PEG-12 DIMETHICONE/PPG-20 CROSSPOLYMER; ORANGE OIL; WATER; SILICON DIOXIDE; LAVANDIN OIL; BUTYLOCTYL SALICYLATE; CAPRYLYL TRISILOXANE; POLYMETHYLSILSESQUIOXANE (11 MICRONS); ETHYLHEXYL PALMITATE; DIMETHYL ISOSORBIDE; .ALPHA.-TOCOPHEROL ACETATE; SHEA BUTTER; CERAMIDE 3; EDETATE DISODIUM; ERYTHROPOIETIN; GOLD; WINE GRAPE; BERGAMOT OIL; MALUS DOMESTICA WHOLE; DIACETYL BOLDINE; PHENOXYETHANOL; LECITHIN, SOYBEAN; SESAME OIL; ISODODECANE; MEDIUM-CHAIN TRIGLYCERIDES; AZADIRACHTA INDICA BARK; XANTHAN GUM; MORINGA OLEIFERA SEED OIL; ISOMALT; TOCOPHEROL

3 LAB WW Day SPF 40

Active Ingredients

Homosalate 10%

Octisalate 5%

Avobenzone 3.0%

Octocrylene 2.6%

Purpose

Sunscreen

USES

- Helps prevent sunburn
- If used as directed with other sun protection measures (see Directions), decreases the risk of skin cancer and early skin aging caused by the sun

WARNINGS

For external use only.

Do not useon damaged or broken skin.

WHEN USING

When using this productkeep out of eyes. Rinse with water to remove

Stop use and ask a doctorif rash occurs.

Keep out of reach of children. If product is swallowed, get medical help or contact a Poison Control Center right away.

DIRECTIONS

- Apply liberally 15 minutes before sun exposure
- Use a water resistant sunscreen if swimming or sweating
- Reapply at least every 2 hours
- Children under 6 months: Ask a doctor
- Apply to all skin exposed to the sun

OTHER INFORMATION

Protect this product from excessive heat and direct sun

Inactive Ingredients

Isododecane, Dimethicone/ Bis-Isobutyl PPG-20 Crosspolymer, Ethylhexyl Palmitate, Butyloctyl Salicylate, Caprylyl Methicone, Polymethylsilsesquioxane, Caprylic/Capric Triglyceride, Dimethicone/Vinyl Dimethicone Crosspolymer, Water, Glycerin, PEG-12 Dimethicone/PPG-20 Crosspolymer, Silica, Melia Azadirachta Extract, Sesamum Indicum (Sesame) Seed Oil, Moringa Oleifera Seed Oil, Olea Europaea (Olive) Fruit Oil, Oligopeptide-4, Oligopeptide-5, sh-Polypeptide-7, Acetyl Heptapeptide-9, Isomalt, Vitis Vinifera (Grape) Fruit Cell Extract, Malus Domestica Fruit Cell Culture Extract, Lecithin, Xanthan Gum, Hydrolyzed Pea Protein, Squalane, Phytosterols, Ceramide NP, Butyrospermum Parkii (Shea) Butter, Tocopherol, Tocopheryl Acetate, Diacetyl Boldine, Phenoxyethanol, Dimethyl Isosorbide, Sodium Phosphate, Disodium EDTA, Colloidal Gold, Citrus Aurantium Dulcis (Orange) Peel Oil, Citrus Aurantium Bergamia (Bergamot) Fruit Oil, Lavandula Hybrida Oil